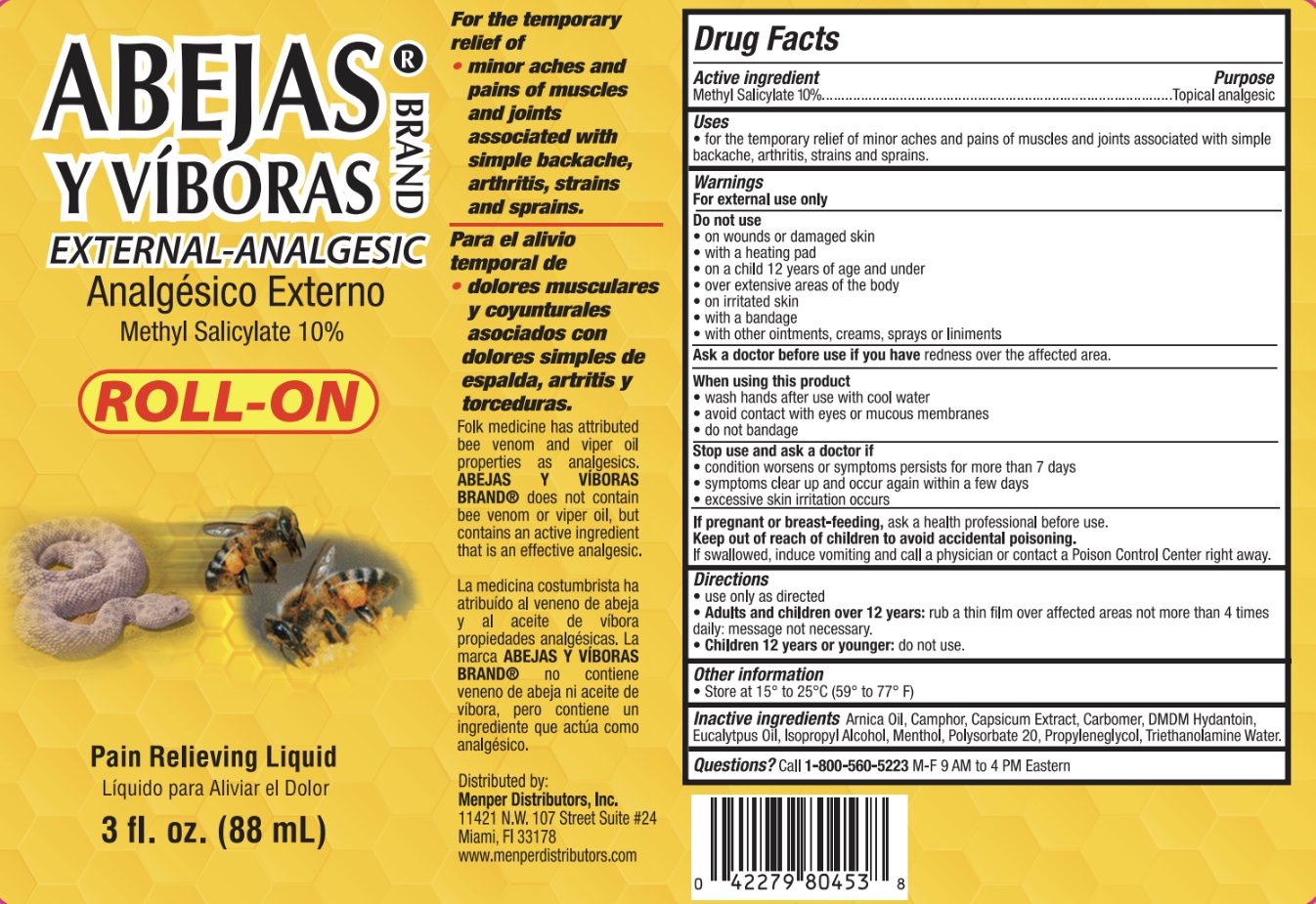 DRUG LABEL: Abejas y Viboras Roll On
NDC: 53145-705 | Form: LIQUID
Manufacturer: Menper Distributors Inc.
Category: otc | Type: HUMAN OTC DRUG LABEL
Date: 20250722

ACTIVE INGREDIENTS: METHYL SALICYLATE 10 g/100 g
INACTIVE INGREDIENTS: WATER; POLYSORBATE 20; ARNICA MONTANA FLOWER; CAMPHOR OIL; PROPYLENE GLYCOL; POLYACRYLIC ACID (250000 MW); DMDM HYDANTOIN; EUCALYPTUS OIL; CAPSICUM; TROLAMINE; MENTHOL; ISOPROPYL ALCOHOL

Abejas y Vivoras Roll On

Active ingredient and Purpose

Active ingredient | Purpose
Methyl salicylate 10% .................... | Topical analgesic

Uses

For the temporary relief of minor aches and pains of muscles and joints associated with

- simple backache
- arthritis
- strains
- sprains

Warnings

For external use only.

Do not use

- on wounds or damaged skin
- with a heating pad
- on a child 12 years o age and under
- over estensive areas of the body
- on irritated skin
- with a bandage
- with other ointments, creams, sprays or liniments

Ask a doctor before use if you have

- redness over the affected area

When using this product

- wash hands after use with cool water
- avoid contact with eyes or mucous membranes
- do not bandage

Stop use and ask a doctor if

- condition worsens or symptoms persist for more than 7 days
- symptoms clear up and and occur again within a few days
- excessive skin irritation occurs

If pregnant or breast-feeding,

ask a health professional before use.

Keep out of reach of children to avoid accidental poisoning.

If swallowed, induce vomiting and call a physicaian or contact a Poision Control Center right away.

Directions

- use only as directed
- adults and children over 12 years:rub a thin film over affected areas not more than 4 times daily
- children 12 years or younger:do not use

Other information

- store at 15°–25°C(59°– 77°F)

Inactive ingredients

arnica oil, camphor, capsicum extract, carbomer, dmdm hydantoin, eucalyptus oil, isopropyl alcohol, menthol, polysorbate 20, propylene glycol, triethanolamine, water

Questions?

1-800-560-5223M-F 9AM – 4 PM Eastern

Principal Display Panel

Abejas y Viboras

External Analgesic Cream

Methyl Salicylate 10%

ROLL-ON

Pain Relieving Luquid

3 fl oz (88mL)